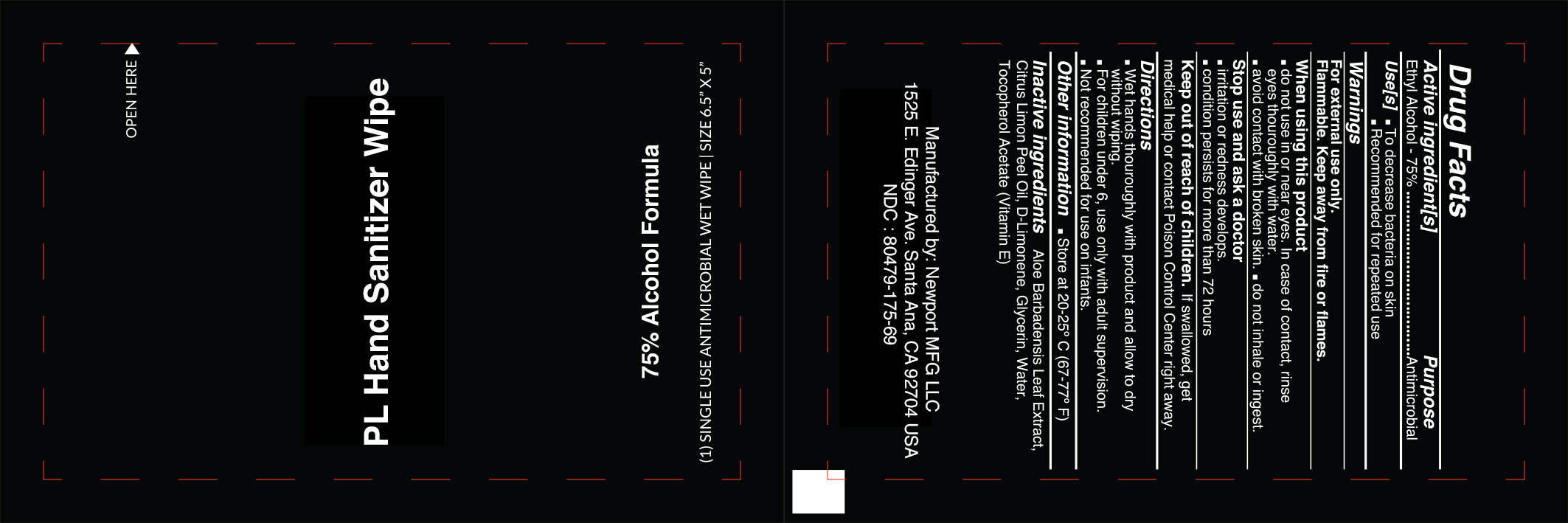 DRUG LABEL: PL Hand Sanitizer Wipe
NDC: 80479-275 | Form: CLOTH
Manufacturer: Newport MFG LLC
Category: otc | Type: HUMAN OTC DRUG LABEL
Date: 20201021

ACTIVE INGREDIENTS: ALCOHOL 75 mL/100 mL
INACTIVE INGREDIENTS: .ALPHA.-TOCOPHEROL ACETATE; LEMON OIL; LIMONENE, (+)-; GLYCERIN; WATER; ALOE VERA LEAF

PL Hand Sanitizer Wipe

Active Ingredient(s)

Ethyl Alcohol 75% v/v. Purpose: Antimicrobial

Purpose

Antimicrobial

Use

- To decrease bacteria on skin
- Recommended for repeated use

Warnings

For external use only. Flammable. Keep away from heat or flame

Do not use

- in children less than 2 months of age
- on open skin wounds

When using this product keep out of eyes, ears, and mouth. In case of contact with eyes, rinse eyes thoroughly with water.
Stop use and ask a doctor if irritation or rash occurs. These may be signs of a serious condition.
Keep out of reach of children. If swallowed, get medical help or contact a Poison Control Center right away.

Stop use and ask a doctor if irritation or rash occurs. These may be signs of a serious condition.

Keep out of reach of children. If swallowed, get medical help or contact a Poison Control Center right away.

Directions

- Wet hands thouroughly with product and allow to dry without wiping.
- for children under 5, use only with adult supervision.
- not recommended for use on infants

Other information

- Store between 20-25C (67-77F)

Inactive ingredients

Aloe Barbadensis Leaf Extract, Citrus Limon Peel Oil, D-Limonene, Glycerin, Tocopherol Acetate (Vitamin E), Water

Package Label - Principal Display Panel

3 mL NDC: 80479-275-69